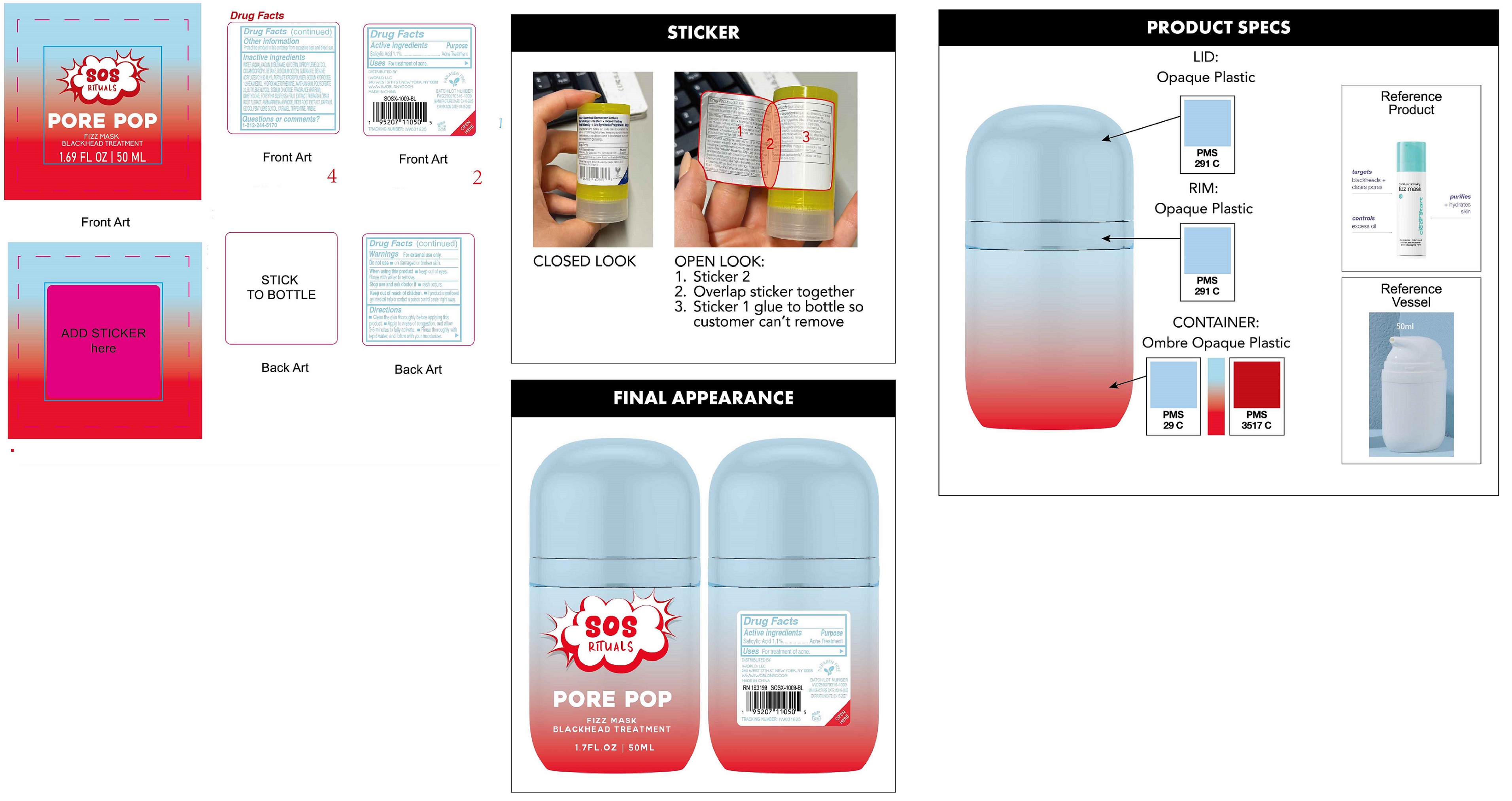 DRUG LABEL: SOS Rituals Pore Pop Fizz Mask Blackhead Treatment
NDC: 85179-008 | Form: LOTION
Manufacturer: I World LLC
Category: otc | Type: HUMAN OTC DRUG LABEL
Date: 20250317

ACTIVE INGREDIENTS: SALICYLIC ACID 11 mg/1 mL
INACTIVE INGREDIENTS: WATER; KAOLIN; DISILOXANE; GLYCERIN; DIPROPYLENE GLYCOL; COCAMIDOPROPYL BETAINE; DISODIUM COCOYL GLUTAMATE; BETAINE; SODIUM HYDROXIDE; 1,2-HEXANEDIOL; HYDROXYACETOPHENONE; XANTHAN GUM; POLYSORBATE 20; BUTYLENE GLYCOL; SODIUM CHLORIDE; DIMETHICONE; FORSYTHIA SUSPENSA FRUIT; PUERARIA MONTANA VAR. LOBATA ROOT; ANEMARRHENA ASPHODELOIDES ROOT; CARAMEL; TURPENTINE; PINENE

SOS Rituals Pore Pop Fizz Mask Blackhead Treatment

Active ingredients

Salicylic Acid 1.1%

Purpose

Acne Treatment

Uses

For treatment of acne.

Warnings

For external use only.

Do not use

- on damaged or broken skin.

When using this product

- Keep out of eyes. Rinse with water to remove.

Stop use and ask doctor if

- rash occurs.

Keep out of reach of children.

- If product is swallowed get medical help or contact a poison control center right away.

Directions

- Clean the skin thoroughly before applying this product.
- Apply to areas of congestion, and allow 3-5 minutes to fully activate.
- Rinse thoroughly with tepid water, and follow with your moisturizer.

Other information

Protect the product in this container from excessive heat and direct sun.

Inactive ingredients

WATER (AQUA), KAOLIN, DISILOXANE, GLYCERIN, DIPROPYLENE GLYCOL, COCAMIDOPROPYL BETAINE, DISODIUM COCOYL GLUTAMATE, BETAIN, ACRYLATES/C10-30 ALKYL ACRYLATE CROSSPOLYMER, SODIUM HYDROXIDE, 1,2-HEXANEDIOL, HYDROXYACETOPHENONE, XANTHAN GUM, POLYSORBATE 20, BUTYLENE GLYCOL, SODIUM CHLORIDE, FRAGRANCE (PARFUM), DIMETHICONE, FORSYTHIA SUSPENSA FRUIT EXTRACT, PUERARIA LOBATA ROOT EXTRACT, ANEMARRHENA ASPHODELOIDES ROOT EXTARCT, CAPRYLYL GLYCOL PENITYLRNR GLYCOL, CARAMEL, TURPENTINE, PINENE.

Questions or comments?

1-212-244-5170